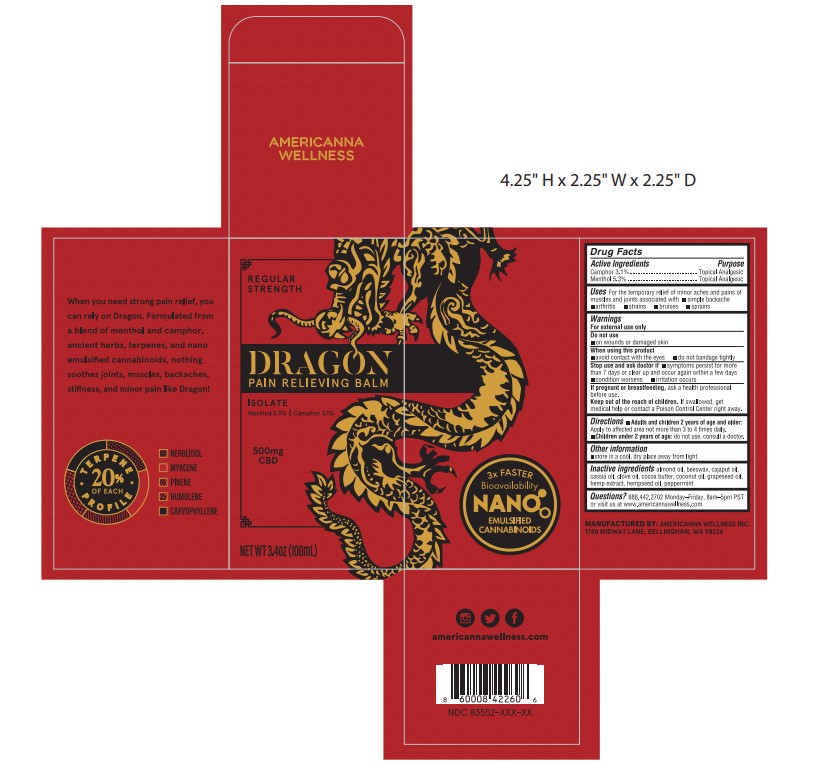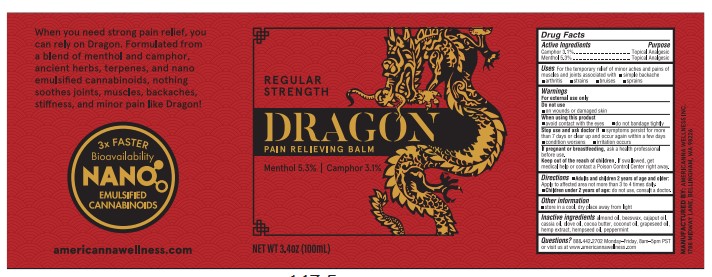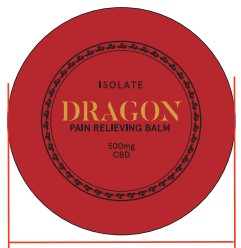 DRUG LABEL: Dragon Pain Relieving Balm
NDC: 83552-105 | Form: SALVE
Manufacturer: Americanna Wellness, Inc.
Category: otc | Type: HUMAN OTC DRUG LABEL
Date: 20251124

ACTIVE INGREDIENTS: MENTHOL 5.3 g/100 g; CAMPHOR (SYNTHETIC) 3.1 g/100 g
INACTIVE INGREDIENTS: CHINESE CINNAMON OIL; GRAPE SEED OIL; CAJUPUT OIL; ALMOND OIL; CLOVE OIL; COCONUT OIL; PEPPERMINT; YELLOW WAX; COCOA BUTTER; HEMP; CANNABIS SATIVA SEED OIL

Regular Strength Isolate 3.4 oz

Active ingredients

Camphor 3.1%

Menthol 5.3%

Purpose

Camphor 3.1%.................Topical Analgesic

Menthol 5.3%..................Topical Analgesic

Uses

For the temporary relief of minor aches and pains of muscles and joints associated with

- simple backache
- arthritis
- strains
- bruises
- sprains

Warnings

For external use only

Do not use

- on wounds or damaged skin

When using this product

- avoid contact with the eyes
- do not bandage tightly

Stop use and ask doctor if

- symptoms persist for more than 7 days or clear up and occur again within a few days
- condition worsens
- irritation occurs

PREGNANCY OR BREAST FEEDING

If pregnant or breastfeeding,ask a health professional before use.

Keep out of reach of children.If swallowed, get medical help or contact a Poison Control Center right away.

Directions

- Adults and children 2 years of age and older: Apply to affected area not more than 3 to 4 times daily.
- Children under 2 years of age:do not use, consult a doctor.

Other information

- store in a cool, dry place away from light

Inactive ingredients

almond oil, beeswax, cajaput oil, cassia oil, clove oil, cocoa butter, coconut oil, grapeseed oil, hemp extract, hempseed oil, peppermint

Questions?

888.442.2707 Monday-Friday, 8am-5pm PST or visit us at www.americannawellness.com

PACKAGE LABEL

Regular Strength

DRAGON Pain Relieving Balm

Isolate

Menthol 5.3% | Camphor 3.1%

500mg CBD

Net Wt 3.4oz (100mL)